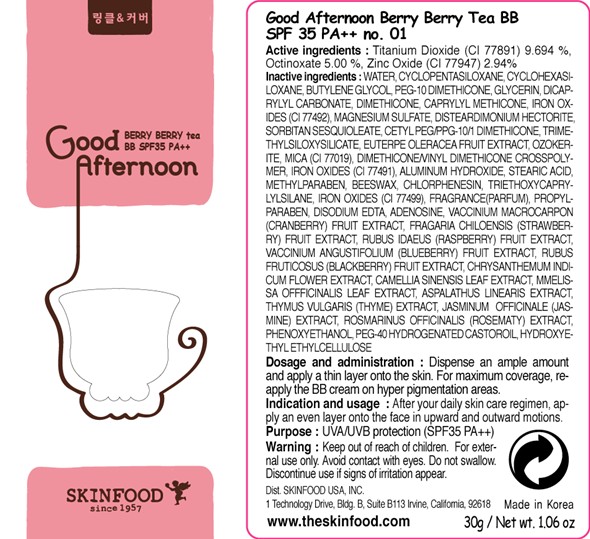 DRUG LABEL: GOOD AFTERNOON BERRY BERRY TEA BB
NDC: 76214-044 | Form: CREAM
Manufacturer: SKINFOOD CO., LTD.
Category: otc | Type: HUMAN OTC DRUG LABEL
Date: 20111117

ACTIVE INGREDIENTS: TITANIUM DIOXIDE 2.90 g/30 g; OCTINOXATE 1.50 g/30 g; ZINC OXIDE 0.88 g/30 g
INACTIVE INGREDIENTS: WATER; CYCLOMETHICONE 5; CYCLOMETHICONE 6; BUTYLENE GLYCOL; GLYCERIN; DICAPRYLYL CARBONATE; DIMETHICONE; MICA; SORBITAN SESQUIOLEATE; ACAI; ALUMINUM HYDROXIDE; STEARIC ACID; METHYLPARABEN; YELLOW WAX; CHLORPHENESIN; TRIETHOXYCAPRYLYLSILANE; PROPYLPARABEN; EDETATE DISODIUM; ADENOSINE; CRANBERRY; BEACH STRAWBERRY; RASPBERRY; BLACKBERRY; DENDRANTHEMA INDICUM FLOWER; GREEN TEA LEAF; MELISSA OFFICINALIS LEAF; THYME; JASMINUM OFFICINALE FLOWER; ROSEMARY; PHENOXYETHANOL; POLYOXYL 40 HYDROGENATED CASTOR OIL

Drug Facts

ACTIVE INGREDIENT

Active ingredients: Titanium Dioxide 9.694 %, Octinoxate 5.00 %, Zinc Oxide 2.94%

Inactive ingredients:
Water, Cyclopentasiloxane, Cyclohexasiloxane, Butylene Glycol, PEG-10 Dimethicone, Glycerin, Dicaprylyl Carbonate, Dimethicone, Caprylyl Methicone, Iron Oxides (CI 77492), Magnesium Sulfate, Mica (CI 77019), Disteardimonium Hectorite, Sorbitan Sesquioleate, Cetyl PEG/PPG-10/1 Dimethicone, Trimethylsiloxysilicate, Euterpe Oleracea Fruit Extract, Ozokerite, Dimethicone/Vinyl Dimethicone Crosspolymer, Aluminum Hydroxide, Iron Oxides (CI 77491), Stearic Acid, Methylparaben, Beeswax, Chlorphenesin, Triethoxycaprylylsilane, Fragrance(Parfum), Iron Oxides (CI 77499), Propylparaben, Disodium EDTA, Adenosine, Vaccinium Macrocarpon (Cranberry) Fruit Extract, Fragaria Chiloensis (Strawberry) Fruit Extract, Rubus Idaeus (Raspberry) Fruit Extract, Vaccinium Angustifolium (Blueberry) Fruit Extract, Rubus Fruticosus (Blackberry) Fruit Extract, Chrysanthemum Indicum Flower Extract, Camellia Sinensis Leaf Extract, Melissa Officinalis Leaf Extract, Aspalathus Linearis Extract, Thymus Vulgaris (Thyme) Extract, Jasminum Officinale (Jasmine) Extract, Rosmarinus Officinalis (Rosemary) Extract, Phenoxyethanol, PEG-40 Hydrogenated Castor Oil, Hydroxyethyl Ethylcellulose

Purpose: UVA/UVB protection

Warnings:
For external use only.
Avoid contact with eyes. Do not swallow.
Discontinue use if signs of irritation appear.

Keep out of reach of children:
Keep out of reach of children.

Indication and usage:
After your daily skin care regimen, apply an even layer onto the face in upward and outward motions.